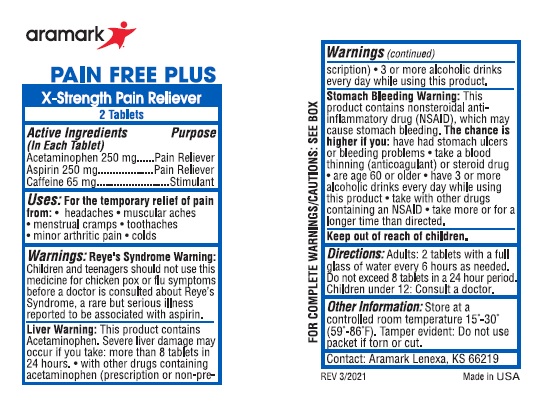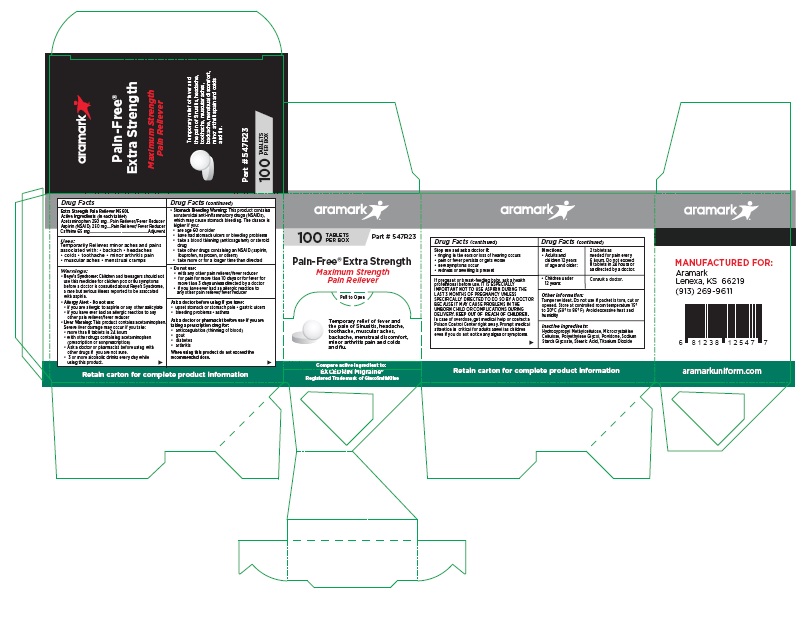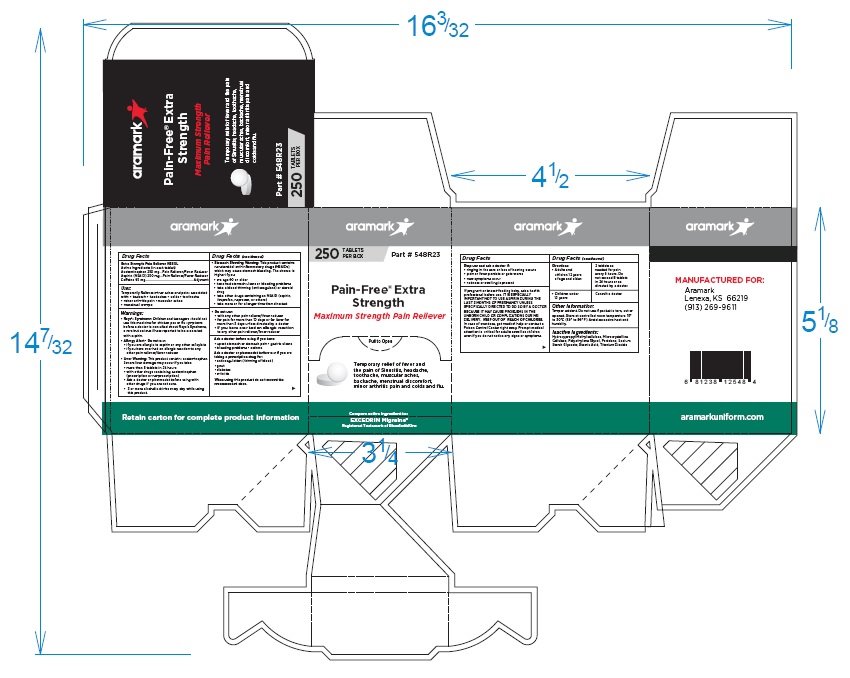 DRUG LABEL: Aramark Pain-Free Extra Strength
NDC: 81238-0560 | Form: TABLET
Manufacturer: Western First Aid Safety DBA Aramark
Category: otc | Type: HUMAN OTC DRUG LABEL
Date: 20210603

ACTIVE INGREDIENTS: ACETAMINOPHEN 250 mg/1 1; ASPIRIN 250 mg/1 1; CAFFEINE 65 mg/1 1
INACTIVE INGREDIENTS: HYPROMELLOSE, UNSPECIFIED; MICROCRYSTALLINE CELLULOSE; POLYETHYLENE GLYCOL, UNSPECIFIED; POVIDONE; SODIUM STARCH GLYCOLATE TYPE A CORN; STEARIC ACID; TITANIUM DIOXIDE

Aramark Pain-Free Extra Strength

Drug Facts

Extra Strength Pain Reliever M560L
Active Ingredients (in each tablet)
Acetaminophen 250 mg
Aspirin (NSAID) 250 mg
Caffeine 65 mg

PURPOSE

Acetaminophen ....Pain Reliever/Fever Reducer
Aspirin (NSAID) ....Pain Reliever/Fever Reducer
Caffeine ...............Adjuvent

Uses:
Temporarily Relieves minor aches and pains
associated with: • backach • headaches
• colds • toothache • minor arthritis pain
• muscular aches • menstrual cramps

Warnings:
• Reye’s Syndrome: Children and teenagers should not
use this medicine for chicken pox or flu symptoms
before a doctor is consulted about Reye’s Syndrome,
a rare but serious illness reported to be associated
with aspirin.
• Allergy Alert - Do not use:
• if you are allergic to aspirin or any other salicylate
• if you have ever had an allergic reaction to any
other pain reliever/fever reducer
• Liver Warning: This product contains acetaminophen.
Severe liver damage may occur if you take:
• more than 8 tablets in 24 hours
• with other drugs containing acetaminophen
(Prescription or nonprescription)
• Ask a doctor or pharmacist before using with
other drugs if you are not sure.
• 3 or more alcoholic drinks every day while
using this product.
• Stomach Bleeding Warning: This product contains
nonsteroidal anti-inflammatory drugs (NSAIDs),
which may cause stomach bleeding. The chance is
higher if you:
• are age 60 or older
• have had stomach ulcers or bleeding problems
• take a blood thinning (anticoagulant) or steroid
drug
• take other drugs containing an NSAID (aspirin,
ibuprofen, naproxen, or others)
• take more or for a longer time than directed

• Do not use:

• with any other pain reliever/fever reducer
• for pain for more than 10 days or for fever for
more than 3 days unless directed by a doctor
• if you have ever had an allergic reaction to
any other pain reliever/fever reducer

Ask a doctor before using if you have:
• upset stomach or stomach pain • gastric ulcers
• bleeding problems • asthma

Ask a doctor or pharmacist before use if you are
taking a prescription drug for:
• anticoagulation (thinning of blood)
• gout
• diabetes
• arthritis

When using this product do not exceed the
recommended dose.

Stop use and ask a doctor if:
• ringing in the ears or loss of hearing occurs
• pain or fever persists or gets worse
• new symptoms occur
• redness or swelling is present

PREGNANCY OR BREAST FEEDING

If pregnant or breast-feeding baby, ask a health
professional before use. IT IS ESPECIALLY
IMPORTANT NOT TO USE ASPIRIN DURING THE
LAST 3 MONTHS OF PREGNANCY UNLESS
SPECIFICALLY DIRECTED TO DO SO BY A DOCTOR
BECAUSE IT MAY CAUSE PROBLEMS IN THE
UNBORN CHILD OR COMPLICATIONS DURING
DELIVERY.

Keep out of reach of children. In case of overdose,
get medical help or contact a Poison Control Center
right away. Prompt medical attention is critical for
adults as well as for children even if you do not
notice any signs or symptoms.

DOSAGE AND ADMINISTRATION

Directions: • Adults and children 12 years of age and older: | 2 tablets as needed for pain every 6 hours. Do not exceed 8 tablets in 24 hours or as directed by a doctor.
• Children under 12 years: | Consult a doctor.

Other information:
read all warnings and directions before use. Keep
carton. Store at 20-25°C (68-77°F) avoid excessive
heat above 40°C (104°F)

Inactive Ingredients:
Hydroxypropyl Methylcellulose, Microcrystalline
Cellulose, Polyethylene Glycol, Povidone, Sodium
Starch Glycoate, Stearic Acid, Titanium Dioxide

Package Labeling

aramark

100 TABLETS Part # 547R23
PER BOX

Pain-Free® Extra Strength
Maximum Strength
Pain Reliever

Temporary relief of fever and
the pain of Sinusitis, headache,
toothache, muscular aches,
backache, menstrual discomfort,
minor arthritis pain and colds
and flu.

Compare active ingredient to:
EXCEDRIN Migraine®
Registered Trademark of GlaxoSmithKline

MANUFACTURED FOR:

Aramark
Lenexa, KS 66219
(913) 269-9611

aramarkuniform.com

Retain carton for complete product information

100 Tablet Box

250 Tablet Box

2-Tablet Packet

res